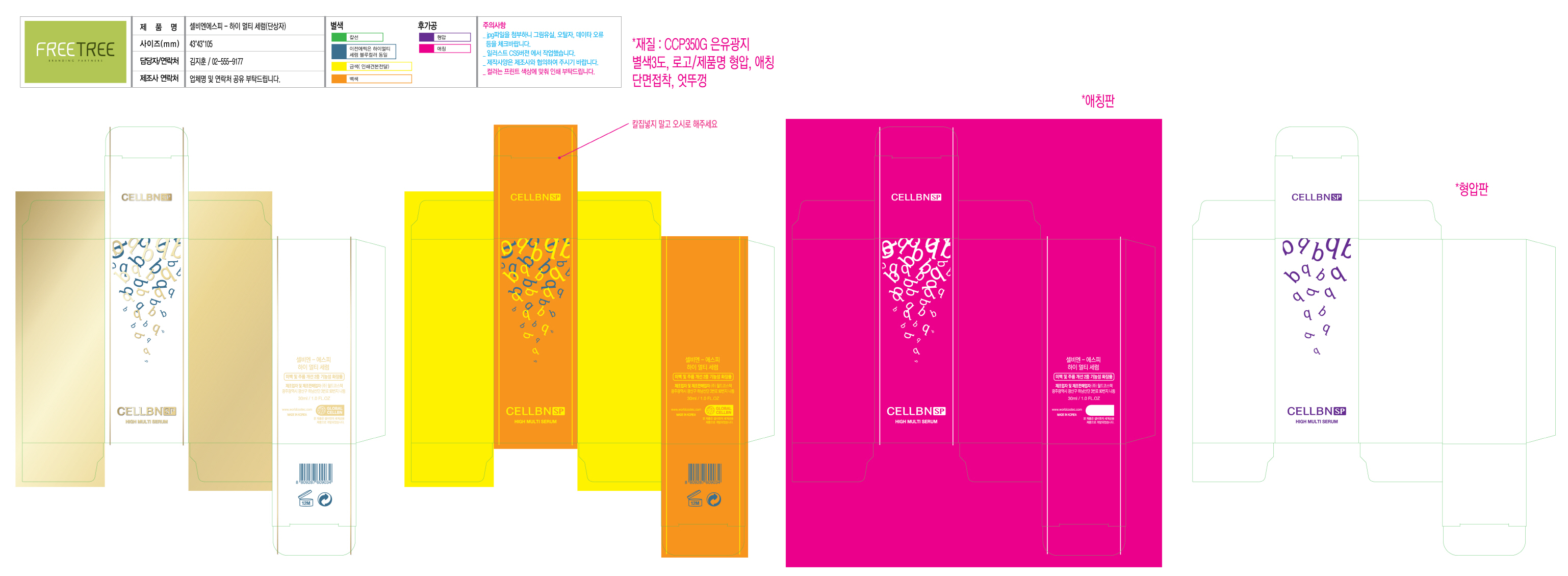 DRUG LABEL: CELLBN SP HIGH MULTI SERUM
NDC: 71450-0008 | Form: GEL
Manufacturer: WORLDCOSTEC.CO.,LTD
Category: otc | Type: HUMAN OTC DRUG LABEL
Date: 20170531

ACTIVE INGREDIENTS: ARBUTIN 2 g/100 mL; ADENOSINE 0.05 g/100 mL
INACTIVE INGREDIENTS: WATER

ACTIVE INGREDIENT

Arbutin, Adenosine

INACTIVE INGREDIENT

Water, Etc

PURPOSE

Skin Protectant - Whitening, Anti-Wrinkle

Keep out of reach of the children

INDICATIONS AND USAGE

Apply to the face and around the neck in the morning and evening

WARNINGS

1. If the following symptoms occur after product use, stop using the product immediately and consult a dermatologist (continuous use can exacerbate the symptoms).
1) Occurrence of red spots, swelling, itchiness, and other skin irritation
2) If the symptoms above occur after the application area is exposed to direct sunlight

2. Do not use on open wounds, eczema, and other skin irritations

3. Precaution for Storage and Handling
1) Close the lid after use
2) Keep out of reach of infants and children
3) Do not to store in a place with high/low temperature and exposed to direct sunlight

4. Use as avoiding eye areas.

DOSAGE AND ADMINISTRATION

for external use only